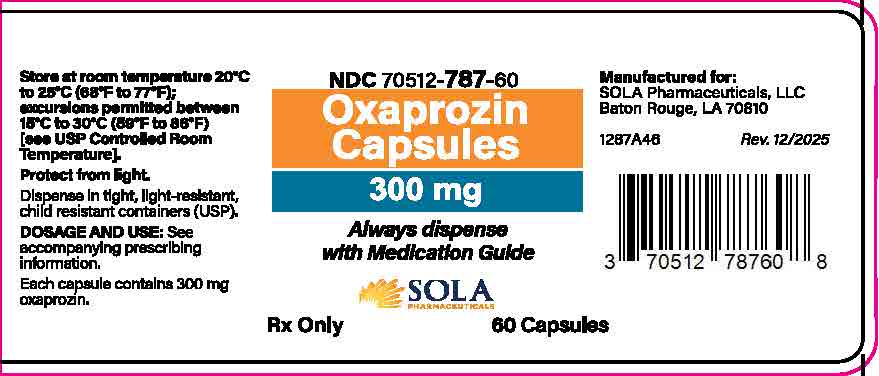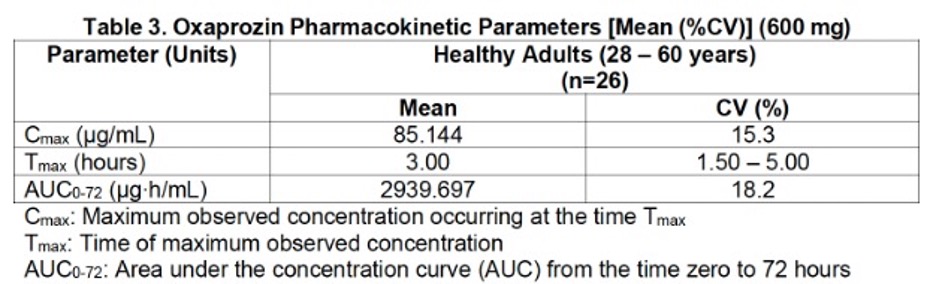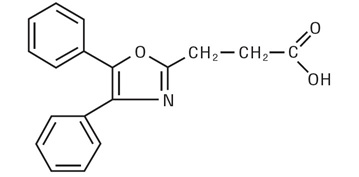 DRUG LABEL: Oxaprozin
NDC: 70512-787 | Form: CAPSULE
Manufacturer: SOLA Pharmaceuticals, LLC
Category: prescription | Type: HUMAN PRESCRIPTION DRUG LABEL
Date: 20251203

ACTIVE INGREDIENTS: OXAPROZIN 300 mg/1 1
INACTIVE INGREDIENTS: MICROCRYSTALLINE CELLULOSE; STARCH, CORN; SODIUM STARCH GLYCOLATE TYPE A; HYPROMELLOSE 2910 (5 MPA.S); STEARIC ACID; SILICON DIOXIDE

HIGHLIGHTS OF PRESCRIBING INFORMATION

These highlights do not include all the information needed to use Oxaprozin safely and effectively. See full prescribing information for OXAPROZIN CAPSULES.
OXAPROZIN CAPSULES, for oral use
Initial U.S. Approval: 1992

Warning: RISK OF SERIOUS CARDIOVASCULAR AND GASTROINTESTINAL EVENTS

See full prescribing information for complete boxed warning.

- Nonsteroidal anti-inflammatory drugs (NSAIDs) cause an increased risk of serious cardiovascular thrombotic events, including myocardial infarction and stroke, which can be fatal. This risk may occur early in treatment and may increase with duration of use (5.1)
- COXANTO is contraindicated in the setting of coronary artery bypass graft (CABG) surgery (4, 5.1)
- NSAIDs cause an increased risk of serious gastrointestinal (GI) adverse events including bleeding, ulceration, and perforation of the stomach or intestines, which can be fatal. These events can occur at any time during use and without warning symptoms. Elderly patients and patients with a prior history of peptic ulcer disease and/or GI bleeding are at greater risk for serious GI events (5.2)

1 INDICATIONS AND USAGE

OXAPROZIN CAPSULES is a non-steroidal anti-inflammatory drug indicated for:

- Relief of signs and symptoms of Osteoarthritis (OA) (1)
- Relief of signs and symptoms of Rheumatoid Arthritis (RA) (1)
- Relief of signs and symptoms of Juvenile Rheumatoid Arthritis (JRA) (1)

2 DOSAGE AND ADMINISTRATION

- Use the lowest effective dosage for shortest duration consistent with individual patient treatment goals (2.1)
- OA: 1200 mg (four 300 mg caplets) given orally once a day (2.2, 2.5, 14.1)
- RA: 1200 mg (four 300 mg caplets) given orally once a day (2.3, 2.5, 14.2)
- JRA: 600 mg (two 300 mg capsules) once daily in patients 22 to 31 kg. 900 mg (three 300 mg capsules) once daily in patients 32 to 54 kg. 1,200 mg (four 300 mg capsules) once daily in patients 55 kg or greater (2.4, 2.5)

3 DOSAGE FORMS AND STRENGTHS

Capsules: 300 mg (3)

4 CONTRAINDICATIONS SECTION

- Known hypersensitivity to oxaprozin or any components of the drug product (4)
- History of asthma, urticaria, or other allergic-type reactions after taking aspirin or other NSAIDs (4)
- In the setting of CABG surgery (4)

5 WARNINGS AND PRECAUTIONS

- Hepatotoxicity: Inform patients of warning signs and symptoms of hepatotoxicity. Discontinue if abnormal liver tests persist or worsen or if clinical signs and symptoms of liver disease develop (5.3)
- Hypertension: Patients taking some antihypertensive medications may have impaired response to these therapies when taking NSAIDs. Monitor blood pressure (5.4, 7)
- Heart Failure and Edema: Avoid use of OXAPROZIN CAPSULES in patients with severe heart failure unless benefits are expected to outweigh risk of worsening heart failure (5.5)
- Renal Toxicity: Monitor renal function in patients with renal or hepatic impairment, heart failure, dehydration, or hypovolemia. Avoid use of OXAPROZIN CAPSULES in patients with advanced renal disease unless benefits are expected to outweigh risk of worsening renal function (5.6)
- Anaphylactic Reactions: Seek emergency help if an anaphylactic reaction occurs (5.7)
- Exacerbation of Asthma Related to Aspirin Sensitivity: OXAPROZIN CAPSULES is contraindicated in patients with aspirin-sensitive asthma. Monitor patients with preexisting asthma (without aspirin sensitivity) (5.8)
- Serious Skin Reactions: Discontinue OXAPROZIN CAPSULES at first appearance of skin rash or other signs of hypersensitivity (5.9)
- Drug Reaction with Eosinophilia and Systemic Symptoms (DRESS): Discontinue and evaluate clinically (5.10)
- Fetal Toxicity: Limit use of NSAIDs, including OXAPROZIN CAPSULES, between about 20 to 30 weeks in pregnancy due to the risk of oligohydramnios/fetal renal dysfunction. Avoid use of NSAIDs in women at about 30 weeks gestation and later in pregnancy due to the risks of oligohydramnios/fetal renal dysfunction and premature closure of the fetal ductus arteriosus (5.11, 8.1)
- Hematologic Toxicity: Monitor hemoglobin or hematocrit in patients with any signs or symptoms of anemia (5.12, 7)

6 ADVERSE REACTIONS

Most common adverse reactions (incidence > 3%) are: constipation, diarrhea, dyspepsia, nausea, rash (6.1)

To report SUSPECTED ADVERSE REACTIONS, contact Solubiomix, LLC at 1-844-551-9911 or FDA at 1-800-FDA-1088 or www.fda.gov/medwatch.

7 DRUG INTERACTIONS

Drugs that Interfere with Hemostasis (e.g., warfarin, aspirin, selective serotonin reuptake inhibitors [SSRIs]/serotonin norepinephrine reuptake inhibitors [SNRIs]): Monitor patients for bleeding who are concomitantly taking OXAPROZIN CAPSULES with drugs that interfere with hemostasis. Concomitant use of OXAPROZIN CAPSULES and analgesic doses of aspirin is not generally recommended (7)
Angiotensin Converting Enzyme (ACE) Inhibitors, Angiotensin Receptor Blockers (ARB), or Beta-Blockers: Concomitant use with OXAPROZIN CAPSULES may diminish the antihypertensive effect of these drugs. Monitor blood pressure (7)
ACE Inhibitors and ARBs: Concomitant use with OXAPROZIN CAPSULES in elderly, volume depleted, or those with renal impairment may result in deterioration of renal function. In such high risk patients, monitor for signs of worsening renal function (7)
Diuretics: NSAIDs can reduce natriuretic effect of furosemide and thiazide diuretics. Monitor patients to assure diuretic efficacy including antihypertensive effects (7)
Digoxin: Concomitant use with OXAPROZIN CAPSULES can increase serum concentration and prolong half-life of digoxin. Monitor serum digoxin levels (7)

8 USE IN SPECIFIC POPULATIONS

Infertility: NSAIDs are associated with reversible infertility. Consider withdrawal of OXAPROZIN CAPSULES in women who have difficulties conceiving (8.3)

See 17 for PATIENT COUNSELING INFORMATION and Medication Guide.

Revised: 8/2024

FULL PRESCRIBING INFORMATION

Warning: RISK OF SERIOUS CARDIOVASCULAR AND GASTROINTESTINAL EVENTS

.

Cardiovascular Thrombotic Events

- Nonsteroidal anti-inflammatory drugs (NSAIDs) cause an increased risk of serious cardiovascular thrombotic events, including myocardial infarction and stroke, which can be fatal. This risk may occur early in treatment and may increase with duration of use [ see Warnings and Precautions (5.1) ].
- OXAPROZIN is contraindicated in the setting of coronary artery bypass graft (CABG) surgery [ see Contraindications (4) and Warnings and Precautions (5.1) ] .

Gastrointestinal Bleeding, Ulceration, and Perforation

- NSAIDs cause an increased risk of serious gastrointestinal (GI) adverse events including bleeding, ulceration, and perforation of the stomach or intestines, which can be fatal. These events can occur at any time during use and without warning symptoms. Elderly patients and patients with a prior history of peptic ulcer disease and/or GI bleeding are at greater risk for serious GI events [ see Warnings and Precautions (5.2) ].

1 INDICATIONS AND USAGE

OXAPROZIN is indicated:

- For relief of the signs and symptoms of osteoarthritis
- For relief of the signs and symptoms of rheumatoid arthritis
- For relief of the signs and symptoms of juvenile rheumatoid arthritis

2 DOSAGE AND ADMINISTRATION

- Use the lowest effective dosage for shortest duration consistent with individual patient treatment goals (2.1)
- OA: 1200 mg (four 300 mg caplets) given orally once a day (2.2, 2.5, 14.1)
- RA: 1200 mg (four 300 mg caplets) given orally once a day (2.3, 2.5, 14.2)
- JRA: 600 mg (two 300 mg capsules) once daily in patients 22 to 31 kg. 900 mg (three 300 mg capsules) once daily in patients 32 to 54 kg. 1,200 mg (four 300 mg capsules) once daily in patients 55 kg or greater (2.4, 2.5)

2.1 General Dosing Instructions

Carefully consider the potential benefits and risks of OXAPROZIN CAPSULES and other treatment options before deciding to use OXAPROZIN CAPSULES. Use the lowest effective dosage for the shortest duration consistent with individual patient treatment goals [see WARNINGS AND PRECAUTIONS (5)].

Different dose strengths and formulations (e.g., capsules, tablets) of oral oxaprozin are not interchangeable. This difference should be taken into consideration when changing strengths or formulations [see Dosage and Administration (2.2, 2.3, 2.4), Cinical Pharmacology (12.3)].
The highest daily dose for OXAPROZIN CAPSULES is 1,200 mg a day.

2.2 Osteoarthritis

For OA, the dosage is 1,200 mg (four 300 mg capsules) given orally once a day [see DOSAGE AND ADMINISTRATION (2.5)].

2.3 Rheumatoid Arthritis

For RA, the dosage is 1,200 mg (four 300 mg capsules) given orally once a day [see DOSAGE AND ADMINISTRATION (2.5)].

2.4 Juvenile Rheumatoid Arthritis

For JRA, in patients 6 to 16 years of age, the recommended dosage given orally once per day should be based on body weight of the patient as given in Table 1 [see DOSAGE AND ADMINISTRATION (2.5)].

Table 1. Recommended Daily Dose of OXAPROZIN CAPSULES by Body Weight in Pediatric Patients

Body Weight Range (kg) | Dose (mg) | Number of Capsules
22 to 31 kg | 600mg | Two capsules
32 to 54 kg | 900mg | Three capsules
2 to 54 kg | 1,200mg | Four capsules

2.5 Individualization of Dosage

After observing the response to initial therapy with OXAPROZIN CAPSULES, the dose and frequency should be adjusted to suit an individual patient's needs. In osteoarthritis and rheumatoid arthritis and juvenile rheumatoid arthritis, the dosage should be individualized to the lowest effective dose of OXAPROZIN CAPSULES to minimize adverse effects. The maximum recommended total daily dose of OXAPROZIN CAPSULES in adults and pediatric patients is 1,200 mg.

Patients with low body weight should initiate therapy with 600 mg once daily. Patients with severe renal impairment or on dialysis should also initiate therapy with 600 mg once daily. If there is insufficient relief of symptoms in such patients, the dose may be cautiously increased to 1,200 mg, but only with close monitoring [see CLINICAL PHARMACOLOGY (12.3)].

Physicians should ensure that patients are tolerating lower doses without gastroenterologic, renal, hepatic, or dermatologic adverse effects before advancing to larger doses. Most patients will tolerate once-a-day dosing with OXAPROZIN CAPSULES, although divided doses may be tried in patients unable to tolerate single doses.

3 DOSAGE FORMS AND STRENGTHS

OXAPROZIN CAPSULES (oxaprozin) capsules: 300 mg capsules, white opaque capsule imprinted “403” on the cap in black ink

4 CONTRAINDICATIONS SECTION

OXAPROZIN CAPSULES is contraindicated in the following patients:

- Known hypersensitivity (e.g., anaphylactic reactions and serious skin reactions) to oxaprozin or any components of the drug product [see WARNINGS AND PRECAUTIONS (5.7, 5.9)]
- History of asthma, urticaria, or other allergic-type reactions after taking aspirin or other NSAIDs. Severe, sometimes fatal, anaphylactic reactions to NSAIDs have been reported in such patients [see WARNINGS AND PRECAUTIONS (5.7, 5.8)]
- In the setting of CABG surgery [see WARNINGS AND PRECAUTIONS (5.1)]

5 WARNINGS AND PRECAUTIONS

.

5.1 Cardiovascular Thrombotic Events

Clinical trials of several cyclooxygenase-2 (COX-2) selective and nonselective NSAIDs of up to three years duration have shown an increased risk of serious cardiovascular (CV) thrombotic events, including myocardial infarction (MI) and stroke, which can be fatal. Based on available data, it is unclear that the risk for CV thrombotic events is similar for all NSAIDs. The relative increase in serious CV thrombotic events over baseline conferred by NSAID use appears to be similar in those with and without known CV disease or risk factors for CV disease. However, patients with known CV disease or risk factors had a higher absolute incidence of excess serious CV thrombotic events, due to their increased baseline rate. Some observational studies found that this increased risk of serious CV thrombotic events began as early as the first weeks of treatment. The increase in CV thrombotic risk has been observed most consistently at higher doses.

To minimize the potential risk for an adverse CV event in NSAID-treated patients, use the lowest effective dose for the shortest duration possible. Physicians and patients should remain alert for the development of such events, throughout the entire treatment course, even in the absence of previous CV symptoms. Patients should be informed about the symptoms of serious CV events and the steps to take if they occur.

There is no consistent evidence that concurrent use of aspirin mitigates the increased risk of serious CV thrombotic events associated with NSAID use. The concurrent use of aspirin and an NSAID, such as oxaprozin, increases the risk of serious gastrointestinal (GI) events [see WARNINGS AND PRECAUTIONS (5.2)].

Status Post Coronary Artery Bypass Graft (CABG) Surgery

Two large, controlled clinical trials of a COX-2 selective NSAID for the treatment of pain in the first 10 to 14 days following CABG surgery found an increased incidence of myocardial infarction and stroke. NSAIDs are contraindicated in the setting of CABG [see CONTRAINDICATIONS (4)].

Post-MI Patients

Observational studies conducted in the Danish National Registry have demonstrated that patients treated with NSAIDs in the post-MI period were at increased risk of reinfarction, CV-related death, and all-cause mortality beginning in the first week of treatment. In this same cohort, the incidence of death in the first year post-MI was 20 per 100 person years in NSAID-treated patients compared to 12 per 100 person years in non-NSAID exposed patients. Although the absolute rate of death declined somewhat after the first year post-MI, the increased relative risk of death in NSAID users persisted over at least the next four years of follow-up.

Avoid the use of OXAPROZIN CAPSULES in patients with a recent MI unless the benefits are expected to outweigh the risk of recurrent CV thrombotic events. If OXAPROZIN CAPSULES is used in patients with a recent MI, monitor patients for signs of cardiac ischemia.

5.2 Gastrointestinal Bleeding, Ulceration, and Perforation

NSAIDs, including OXAPROZIN CAPSULES, cause serious gastrointestinal (GI) adverse events including inflammation, bleeding, ulceration, and perforation of the esophagus, stomach, small intestine, or large intestine, which can be fatal. These serious adverse events can occur at any time, with or without warning symptoms, in patients treated with NSAIDs. Only one in five patients, who develop a serious upper GI adverse event on NSAID therapy, is symptomatic. Upper GI ulcers, gross bleeding, or perforation caused by NSAIDs occurred in approximately 1% of patients treated for 3 to 6 months, and in about 2% to 4% of patients treated for one year. However, even short-term NSAID therapy is not without risk.

Risk Factors for GI Bleeding, Ulceration, and Perforation

Patients with a prior history of peptic ulcer disease and/or GI bleeding who used NSAIDs had a greater than 10-times increased risk for developing a GI bleed compared to patients without these risk factors. Other factors that increase the risk of GI bleeding in patients treated with NSAIDs include longer duration of NSAID therapy; concomitant use of oral corticosteroids, antiplatelet drugs (such as aspirin), anticoagulants, or selective serotonin reuptake inhibitors (SSRIs); smoking; use of alcohol; older age; and poor general health status. Most postmarketing reports of fatal GI events occurred in elderly or debilitated patients. Additionally, patients with advanced liver disease and/or coagulopathy are at increased risk for GI bleeding.

Strategies to Minimize the GI Risks in NSAID-treated patients:

- Use the lowest effective dosage for the shortest possible duration.
- Avoid administration of more than one NSAID at a time.
- Avoid use in patients at higher risk unless benefits are expected to outweigh the increased risk of bleeding. For such patients, as well as those with active GI bleeding, consider alternate therapies other than NSAIDs.
- Remain alert for signs and symptoms of GI ulceration and bleeding during NSAID therapy.
- If a serious GI adverse event is suspected, promptly initiate evaluation and treatment, and discontinue OXAPROZIN CAPSULES until a serious GI adverse event is ruled out.
- In the setting of concomitant use of low-dose aspirin for cardiac prophylaxis, monitor patients more closely for evidence of GI bleeding [see DRUG INTERACTIONS (7)].

5.3 Hepatotoxicity

Elevations of alanine aminotransferase (ALT) or aspartate aminotransferase (AST) (three or more times the upper limit of normal [ULN]) have been reported in approximately 1% of NSAID-treated patients in clinical trials. In addition, rare, sometimes fatal, cases of severe hepatic injury, including fulminant hepatitis, liver necrosis, and hepatic failure have been reported.

Elevations of ALT or AST (less than three times ULN) may occur in up to 15% of patients treated with NSAIDs including oxaprozin.

Inform patients of the warning signs and symptoms of hepatotoxicity (e.g., nausea, fatigue, lethargy, diarrhea, pruritus, jaundice, right upper quadrant tenderness, and "flu-like" symptoms). If clinical signs and symptoms consistent with liver disease develop, or if systemic manifestations occur (e.g., eosinophilia, rash), discontinue OXAPROZIN CAPSULES immediately, and perform a clinical evaluation of the patient.

5.4 Hypertension

NSAIDs, including OXAPROZIN CAPSULES, can lead to new onset of hypertension or worsening of preexisting hypertension, either of which may contribute to the increased incidence of CV events. Patients taking angiotensin converting enzyme (ACE) inhibitors, thiazide diuretics, or loop diuretics may have impaired response to these therapies when taking NSAIDs [see DRUG INTERACTIONS (7)].

Monitor blood pressure (BP) during the initiation of NSAID treatment and throughout the course of therapy.

5.5 Heart Failure and Edema

The Coxib and traditional NSAID Trialists' Collaboration meta-analysis of randomized controlled trials demonstrated an approximately two-fold increase in hospitalizations for heart failure in COX-2 selective-treated patients and nonselective NSAID-treated patients compared to placebo-treated patients. In a Danish National Registry study of patients with heart failure, NSAID use increased the risk of MI, hospitalization for heart failure, and death.

Additionally, fluid retention and edema have been observed in some patients treated with NSAIDs. Use of oxaprozin may blunt the CV effects of several therapeutic agents used to treat these medical conditions (e.g., diuretics, ACE inhibitors, or angiotensin receptor blockers [ARBs]) [see DRUG INTERACTIONS (7)].

Avoid the use of OXAPROZIN CAPSULES in patients with severe heart failure unless the benefits are expected to outweigh the risk of worsening heart failure. If OXAPROZIN CAPSULES is used in patients with severe heart failure, monitor patients for signs of worsening heart failure.

5.6 Renal Toxicity and Hyperkalemia

Renal Toxicity

Long-term administration of NSAIDs has resulted in renal papillary necrosis and other renal injury.

Renal toxicity has also been seen in patients in whom renal prostaglandins have a compensatory role in the maintenance of renal perfusion. In these patients, administration of an NSAID may cause a dose-dependent reduction in prostaglandin formation and, secondarily, in renal blood flow, which may precipitate overt renal decompensation. Patients at greatest risk of this reaction are those with impaired renal function, dehydration, hypovolemia, heart failure, liver dysfunction, those taking diuretics and ACE inhibitors or ARBs, and the elderly. Discontinuation of NSAID therapy is usually followed by recovery to the pretreatment state.

No information is available from controlled clinical studies regarding the use of OXAPROZIN CAPSULES in patients with advanced renal disease. The renal effects of OXAPROZIN CAPSULES may hasten the progression of renal dysfunction in patients with preexisting renal disease.

Correct volume status in dehydrated or hypovolemic patients prior to initiating OXAPROZIN CAPSULES. Monitor renal function in patients with renal or hepatic impairment, heart failure, dehydration, or hypovolemia during use of OXAPROZIN CAPSULES [see DRUG INTERACTIONS (7)]. Avoid the use of OXAPROZIN CAPSULES in patients with advanced renal disease unless the benefits are expected to outweigh the risk of worsening renal function. If OXAPROZIN CAPSULES is used in patients with advanced renal disease, monitor patients for signs of worsening renal function.

Hyperkalemia

Increases in serum potassium concentration, including hyperkalemia, have been reported with use of NSAIDs even in some patients without renal impairment. In patients with normal renal function, these effects have been attributed to a hyporeninemic-hypoaldosteronism state.

5.7 Anaphylactic Reactions

Oxaprozin has been associated with anaphylactic reactions in patients with and without known hypersensitivity to oxaprozin and in patients with aspirin-sensitive asthma [see CONTRAINDICATIONS (4) and WARNINGS AND PRECAUTIONS (5.8)]. Seek emergency help if an anaphylactic reaction occurs.

5.8 Exacerbation of Asthma Related to Aspirin Sensitivity

A subpopulation of patients with asthma may have aspirin-sensitive asthma which may include chronic rhinosinusitis complicated by nasal polyps; severe, potentially fatal bronchospasm; and/or intolerance to aspirin and other NSAIDs. Because cross-reactivity between aspirin and other NSAIDs has been reported in such aspirin-sensitive patients, OXAPROZIN CAPSULES is contraindicated in patients with this form of aspirin sensitivity [see CONTRAINDICATIONS (4)]. When OXAPROZIN CAPSULES is used in patients with preexisting asthma (without known aspirin sensitivity), monitor patients for changes in the signs and symptoms of asthma.

5.9 Serious Skin Reactions

NSAIDs, including oxaprozin, can cause serious skin adverse reactions such as exfoliative dermatitis, Stevens-Johnson Syndrome (SJS), and toxic epidermal necrolysis (TEN), which can be fatal. NSAIDs can also cause fixed drug eruption (FDE). FDE may present as a more severe variant known as generalized bullous fixed drug eruption (GBFDE), which can be life-threatening. These serious events may occur without warning. Inform patients about the signs and symptoms of serious skin reactions, and to discontinue the use of OXAPROZIN CAPSULES at the first appearance of skin rash or any other sign of hypersensitivity. OXAPROZIN CAPSULES is contraindicated in patients with previous serious skin reactions to NSAIDs [see CONTRAINDICATIONS (4)].

5.10 Drug Reaction with Eosinophilia and Systemic Symptoms (DRESS)

Drug Reaction with Eosinophilia and Systemic Symptoms (DRESS) has been reported in patients taking NSAIDs such as OXAPROZIN CAPSULES. Some of these events have been fatal or life-threatening. DRESS typically, although not exclusively, presents with fever, rash, lymphadenopathy, and/or facial swelling. Other clinical manifestations may include hepatitis, nephritis, hematological abnormalities, myocarditis, or myositis. Sometimes symptoms of DRESS may resemble an acute viral infection. Eosinophilia is often present. Because this disorder is variable in its presentation, other organ systems not noted here may be involved. It is important to note that early manifestations of hypersensitivity, such as fever or lymphadenopathy, may be present even though rash is not evident. If such signs or symptoms are present, discontinue OXAPROZIN CAPSULES and evaluate the patient immediately.

5.11 Fetal Toxicity

Premature Closure of Fetal Ductus Arteriosus

Avoid use of NSAIDs, including OXAPROZIN CAPSULES, in pregnant women at about 30 weeks gestation and later. NSAIDs, including OXAPROZIN CAPSULES, increase the risk of premature closure of the fetal ductus arteriosus at approximately this gestational age [SEE USE IN SPECIFIC POPULATIONS (8.1)].

Oligohydramnios/Neonatal Renal Impairment

Use of NSAIDs, including OXAPROZIN CAPSULES, at about 20 weeks gestation or later in pregnancy may cause fetal renal dysfunction leading to oligohydramnios and, in some cases, neonatal renal impairment. These adverse outcomes are seen, on average, after days to weeks of treatment, although oligohydramnios has been infrequently reported as soon as 48 hours after NSAID initiation. Oligohydramnios is often, but not always, reversible with treatment discontinuation. Complications of prolonged oligohydramnios may, for example, include limb contractures and delayed lung maturation. In some postmarketing cases of impaired neonatal renal function, invasive procedures such as exchange transfusion or dialysis were required.

If NSAID treatment is necessary between about 20 weeks and 30 weeks gestation, limit OXAPROZIN CAPSULES use to the lowest effective dose and shortest duration possible. Consider ultrasound monitoring of amniotic fluid if OXAPROZIN CAPSULES treatment extends beyond 48 hours. Discontinue OXAPROZIN CAPSULES if oligohydramnios occurs and follow up according to clinical practice [see USE IN SPECIFIC POPULATIONS (8.1)].

5.12 Hematologic Toxicity

Anemia has occurred in NSAID-treated patients. This may be due to occult or gross blood loss, fluid retention, or an incompletely described effect on erythropoiesis. If a patient treated with OXAPROZIN CAPSULES has any signs or symptoms of anemia, monitor hemoglobin or hematocrit.

NSAIDs, including OXAPROZIN CAPSULES, may increase the risk of bleeding events. Co-morbid conditions such as coagulation disorders or concomitant use of warfarin, other anticoagulants, antiplatelet drugs (e.g., aspirin), SSRIs, and serotonin norepinephrine reuptake inhibitors (SNRIs) may increase this risk. Monitor these patients for signs of bleeding [see DRUG INTERACTIONS (7)].

5.13 Masking of Inflammation and Fever

The pharmacological activity of OXAPROZIN CAPSULES in reducing inflammation, and possibly fever, may diminish the utility of diagnostic signs in detecting infections.

5.14 Laboratory Monitoring

Because serious GI bleeding, hepatotoxicity, and renal injury can occur without warning symptoms or signs, consider monitoring patients on long-term NSAID treatment with a complete blood count (CBC) and a chemistry profile periodically [see WARNINGS AND PRECAUTIONS (5.2, 5.3, 5.6)].

5.15 Photosensitivity

Oxaprozin has been associated with rash and/or mild photosensitivity in dermatologic testing. An increased incidence of rash on sun-exposed skin was seen in some patients in the clinical trials.

6 ADVERSE REACTIONS

The following clinically significant adverse reactions are described elswhere in the labeling:

- Cardiovascular Thrombotic Events [see WARNINGS AND PRECAUTIONS (5.1)]
- GI Bleeding, Ulceration and Perforation [see WARNINGS AND PRECAUTIONS (5.2)]
- Hepatotoxicity [see WARNINGS AND PRECAUTIONS (5.3)]
- Hypertension [see WARNINGS AND PRECAUTIONS (5.4)]
- Heart Failure and Edema [see WARNINGS AND PRECAUTIONS (5.5)]
- Renal Toxicity and Hyperkalemia [see WARNINGS AND PRECAUTIONS (5.6)]
- Anaphylactic Reactions [see WARNINGS AND PRECAUTIONS (5.7)]
- Serious Skin Reactions [see WARNINGS AND PRECAUTIONS (5.9)]
- Hematologic Toxicity [see WARNINGS AND PRECAUTIONS (5.12)]

6.1 Clinical Trials Experience

Because clinical trials are conducted under widely varying conditions, adverse reaction rates observed in the clinical trials of a drug cannot be directly compared to rates in the clinical trials of another drug and may not reflect the rates observed in practice.

Adverse reaction data were derived from patients who received oxaprozin, the active component of OXAPROZIN CAPSULES, in multidose, controlled, and open-label clinical trials. Rates for events from clinical trial experience are based on 2253 patients who took 1,200 mg to 1800 mg of the active component of OXAPROZIN CAPSULES per day in clinical trials. Of these, 1721 patients were treated for at least 1 month, 971 patients for at least 3 months, and 366 patients for more than 1 year.

Incidence Greater than 1%: In clinical trials of oxaprozin, the active component of OXAPROZIN CAPSULES, or in patients taking other NSAIDs, the following adverse reactions occurred at an incidence greater than 1%.

Cardiovascular system: edema.

Digestive system: abdominal pain/distress, anorexia, constipation, diarrhea, dyspepsia, flatulence, gastrointestinal ulcers (gastric/duodenal), gross bleeding/perforation, heartburn, liver enzyme elevations, nausea, vomiting.

Hematologic system: anemia, increased bleeding time.

Nervous system: CNS inhibition (depression, sedation, somnolence, or confusion), disturbance of sleep, dizziness, headache.

Skin and appendages: pruritus, rash.

Special senses: tinnitus.

Urogenital system: abnormal renal function, dysuria or frequency.

Incidence Greater than 1%: The following adverse reactions were reported in clinical trials or in patients taking other NSAIDs.

Body as a whole: appetite changes, death, drug hypersensitivity reactions including anaphylaxis, fever, infection, sepsis.

Cardiovascular system: arrhythmia, blood pressure changes, congestive heart failure, hypertension, hypotension, myocardial infarction, palpitations, tachycardia, syncope, vasculitis.

Digestive system: alteration in taste, dry mouth, eructation, esophagitis, gastritis, glossitis, hematemesis, jaundice, liver function abnormalities including liver failure, stomatitis, hemorrhoidal or rectal bleeding.

Hematologic system: aplastic anemia, ecchymoses, eosinophilia, hemolytic anemia, lymphadenopathy, melena, purpura, thrombocytopenia, leukopenia.

Metabolic system: hyperglycemia, weight changes.

Nervous system: anxiety, asthenia, coma, convulsions, dream abnormalities, drowsiness, hallucinations, insomnia, malaise, meningitis, nervousness, paresthesia, tremors, vertigo, weakness.

Respiratory system: asthma, dyspnea, pulmonary infections, pneumonia, sinusitis, symptoms of upper respiratory tract infection, respiratory depression.

Skin: alopecia, angioedema, urticaria, photosensitivity, sweat.

Special senses: blurred vision, conjunctivitis, hearing decrease.

Urogenital: cystitis, hematuria, increase in menstrual flow, oliguria/ polyuria, proteinuria, renal insufficiency, decreased menstrual flow.

Adverse Reactions in Pediatric Patients with Juvenile Rheumatoid Arthritis
In a 3-month open label study in 59 pediatric patients with juvenile rheumatoid arthritis treated with oxaprozin, the active component of OXAPROZIN CAPSULES, adverse events were reported by 58% of patients. Gastrointestinal symptoms were the most frequently reported adverse effects and occurred at a higher incidence than those historically seen in controlled studies in adults. Of 30 patients who continued treatment for more than 3 months (19 to 48 weeks range total treatment duration), nine (30%) experienced rash on sun-exposed areas of the skin and five of those discontinued treatment.

6.2 Postmarketing Experience

The following adverse reactions have been identified during post approval use of oxaprozin, the active component of OXAPROZIN CAPSULES. Because these reactions are reported voluntarily from a population of uncertain size, it is not always possible to reliably estimate their frequency or establish a causal relationship to drug exposure.

Body as a whole: serum sickness.

Digestive system: hepatitis, pancreatitis.

Hematologic system: agranulocytosis, pancytopenia.

Skin: pseudoporphyria, exfoliative dermatitis, erythema multiforme, Stevens-Johnson syndrome, fixed drug eruption (FDE), toxic epidermal necrolysis (Lyell's syndrome).

Urogenital: acute interstitial nephritis, nephrotic syndrome, acute renal failure.

7 DRUG INTERACTIONS

See TABLE 2 for clinically significant drug interactions with oxaprozin [see CLINICAL PHARMACOLOGY (12.3)].

Table 2: Clinically Significant Drug Interactions with Oxaprozin

Drugs That Interfere with Hemostasis
Clinical Impact: | Oxaprozin and anticoagulants such as warfarin have a synergistic effect on bleeding. The concomitant use of oxaprozin and anticoagulants have an increased risk of serious bleeding compared to the use of either drug alone.; Serotonin release by platelets plays an important role in hemostasis. Case-control and cohort epidemiological studies showed that concomitant use of drugs that interfere with serotonin reuptake and an NSAID may potentiate the risk of bleeding more than an NSAID alone.
Intervention: | Monitor patients with concomitant use of OXAPROZIN CAPSULES with anticoagulants (e.g., warfarin), antiplatelet drugs (e.g., aspirin), SSRIs, and SNRIs for signs of bleeding [see WARNINGS AND PRECAUTIONS (5.12)].
Aspirin
Clinical Impact: | Controlled clinical studies showed that the concomitant use of NSAIDs and analgesic doses of aspirin does not produce any greater therapeutic effect than the use of NSAIDs alone. In a clinical study, the concomitant use of an NSAID and aspirin was associated with a significantly increased incidence of GI adverse reactions as compared to use of the NSAID alone [see WARNINGS AND PRECAUTIONS (5.2)].
Intervention: | Concomitant use of OXAPROZIN CAPSULES and analgesic doses of aspirin is not generally recommended because of the increased risk of bleeding [see WARNINGS AND PRECAUTIONS (5.12)].
Intervention: | OXAPROZIN CAPSULES is not a substitute for low dose aspirin for cardiovascular protection.
ACE Inhibitors, Angiotensin Receptor Blockers, and Beta-Blockers
Clinical Impact: | NSAIDs may diminish the antihypertensive effect of ACE inhibitors, ARBs, or beta-blockers (including propranolol).; In patients who are elderly, volume-depleted (including those on diuretic therapy), or have renal impairment, co-administration of an NSAID with ACE inhibitors or ARBs may result in deterioration of renal function, including possible acute renal failure. These effects are usually reversible.
Intervention: | During concomitant use of OXAPROZIN CAPSULES and ACE inhibitors, ARBs, or beta-blockers, monitor blood pressure to ensure that the desired blood pressure is obtained.; During concomitant use of OXAPROZIN CAPSULES and ACE inhibitors or ARBs in patients who are elderly, volume-depleted, or have impaired renal function, monitor for signs of worsening renal function [see WARNINGS AND PRECAUTIONS (5.6)].; When these drugs are administered concomitantly, patients should be adequately hydrated. Assess renal function at the beginning of the concomitant treatment and periodically thereafter.
Diuretics
Clinical Impact: | Clinical studies, as well as post-marketing observations, showed that NSAIDs reduced the natriuretic effect of loop diuretics (e.g., furosemide) and thiazide diuretics in some patients. This effect has been attributed to the NSAID inhibition of renal prostaglandin synthesis.
Intervention: | During concomitant use of OXAPROZIN CAPSULES with diuretics, observe patients for signs of worsening renal function, in addition to assuring diuretic efficacy including antihypertensive effects [see WARNINGS AND PRECAUTIONS (5.6)].
Digoxin
Clinical Impact: | The concomitant use of oxaprozin with digoxin has been reported to increase the serum concentration and prolong the half-life of digoxin.
Intervention: | During concomitant use of OXAPROZIN CAPSULES and digoxin, monitor serum digoxin levels.
Lithium
Clinical Impact: | NSAIDs have produced elevations in plasma lithium levels and reductions in renal lithium clearance. The mean minimum lithium concentration increased 15%, and the renal clearance decreased by approximately 20%. This effect has been attributed to NSAID inhibition of renal prostaglandin synthesis.
Intervention: | During concomitant use of OXAPROZIN CAPSULES and lithium, monitor patients for signs of lithium toxicity.
Methotrexate
Clinical Impact: | Concomitant use of NSAIDs and methotrexate may increase the risk for methotrexate toxicity (e.g., neutropenia, thrombocytopenia, renal dysfunction) because NSAID administration may result in increased plasma levels of methotrexate, especially in patients receiving high doses of methotrexate.
Intervention: | During concomitant use of OXAPROZIN CAPSULES and methotrexate, monitor patients for methotrexate toxicity.
Cyclosporine
Clinical Impact: | Concomitant use of OXAPROZIN CAPSULES and cyclosporine may increase cyclosporine's nephrotoxicity.
Intervention: | During concomitant use of OXAPROZIN CAPSULES and cyclosporine, monitor patients for signs of worsening renal function.
NSAIDs and Salicylates
Clinical Impact: | Concomitant use of oxaprozin with other NSAIDs or salicylates (e.g., diflunisal, salsalate) increases the risk of GI toxicity, with little or no increase in efficacy [see WARNINGS AND PRECAUTIONS (5.2)].
Intervention: | The concomitant use of oxaprozin with other NSAIDs or salicylates is not recommended.
Pemetrexed
Clinical Impact: | Concomitant use of OXAPROZIN CAPSULES and pemetrexed may increase the risk of pemetrexed-associated myelosuppression, renal, and GI toxicity (see the pemetrexed prescribing information).
Intervention: | During concomitant use of OXAPROZIN CAPSULES and pemetrexed, in patients with renal impairment whose creatinine clearance ranges from 45 to 79 mL/min, monitor for myelosuppression, renal and GI toxicity.
Intervention: | NSAIDs with short elimination half-lives (e.g., diclofenac, indomethacin) should be avoided for a period of two days before, the day of, and two days following administration of pemetrexed.
Intervention: | In the absence of data regarding potential interaction between pemetrexed and NSAIDs with longer half-lives (e.g., meloxicam, nabumetone), patients taking these NSAIDs should interrupt dosing for at least five days before, the day of, and two days following pemetrexed administration.
Corticosteroids
Clinical Impact: | Concomitant use of corticosteroids with OXAPROZIN CAPSULES may increase the risk of GI ulceration or bleeding.
Intervention: | Monitor patients with concomitant use of OXAPROZIN CAPSULES with corticosteroids for signs of bleeding [see WARNINGS AND PRECAUTIONS (5.2)].
Glyburide
Clinical Impact: | While oxaprozin does alter the pharmacokinetics of glyburide, coadministration of oxaprozin to type II non-insulin dependent diabetic patients did not affect the area under the glucose concentration curve nor the magnitude or duration of control.
Intervention: | During concomitant use of OXAPROZIN CAPSULES and glyburide, monitor patient's blood glucose in the beginning phase of cotherapy.

Laboratory Test Interactions

False-positive urine immunoassay screening tests for benzodiazepines have been reported in patients taking OXAPROZIN CAPSULES. This is due to lack of specificity of the screening tests. False-positive test results may be expected for several days following discontinuation of OXAPROZIN CAPSULES therapy. Confirmatory tests, such as gas chromatography/mass spectrometry, will distinguish OXAPROZIN CAPSULES from benzodiazepines.

8 USE IN SPECIFIC POPULATIONS

.

8.1 Pregnancy

Risk Summary

Use of NSAIDs, including OXAPROZIN CAPSULES, can cause premature closure of the fetal ductus arteriosus and fetal renal dysfunction leading to oligohydramnios and, in some cases, neonatal renal impairment. Because of these risks, limit dose and duration of OXAPROZIN CAPSULES use between about 20 and 30 weeks of gestation, and avoid OXAPROZIN CAPSULES use at about 30 weeks of gestation and later in pregnancy (see CLINICAL CONSIDERATIONS, DATA).

Premature Closure of Fetal Ductus Arteriosus

Use of NSAIDs, including OXAPROZIN CAPSULES, at about 30 weeks gestation or later in pregnancy increases the risk of premature closure of the fetal ductus arteriosus.

Oligohydramnios/Neonatal Renal Impairment

Use of NSAIDs at about 20 weeks gestation or later in pregnancy has been associated with cases of fetal renal dysfunction leading to oligohydramnios, and in some cases, neonatal renal impairment.

Data from observational studies regarding other potential embryofetal risks of NSAID use in women in the first or second trimesters of pregnancy are inconclusive. In animal reproduction studies, oral administration of oxaprozin to pregnant rabbits at doses 0.1 times the maximum daily human dose (based on body surface area) resulted in evidence of teratogenicity; however, oral administration of oxaprozin to pregnant mice and rats during organogenesis at doses 0.2 times and 1.6 times the maximum recommended human dose, respectively, revealed no evidence of teratogenicity or embryotoxicity. In rat reproduction studies in which oxaprozin was administered through late gestation failure to deliver and a reduction in live birth index was observed at a dose 1.6 times the maximum recommended human dose (based on body surface area). Based on animal data, prostaglandins have been shown to have an important role in endometrial vascular permeability, blastocyst implantation, and decidualization. In animal studies, administration of prostaglandin synthesis inhibitors such as oxaprozin, resulted in increased pre- and post-implantation loss. Prostaglandins also have been shown to have an important role in fetal kidney development. In published animal studies, prostaglandin synthesis inhibitors have been reported to impair kidney development when administered at clinically relevant doses.

The background risk of major birth defects and miscarriage for the indicated population(s) is unknown. All pregnancies have a background risk of birth defect, loss, or other adverse outcomes. In the U.S. general population, the estimated background risk of major birth defects and miscarriage in clinically recognized pregnancies is 2% to 4% and 15% to 20%, respectively.

Clinical Considerations

Fetal/Neonatal Adverse Reactions

Premature Closure of Fetal Ductus Arteriosus:

Avoid use of NSAIDs in women at about 30 weeks gestation and later in pregnancy, because NSAIDs, including OXAPROZIN CAPSULES, can cause premature closure of the fetal ductus arteriosus (see DATA).

Oligohydramnios/Neonatal Renal Impairment:

If an NSAID is necessary at about 20 weeks gestation or later in pregnancy, limit the use to the lowest effective dose and shortest duration possible. If OXAPROZIN CAPSULES treatment extends beyond 48 hours, consider monitoring with ultrasound for oligohydramnios. If oligohydramnios occurs, discontinue OXAPROZIN CAPSULES and follow up according to clinical practice (see DATA).

Labor or Delivery

There are no studies on the effects of OXAPROZIN CAPSULES during labor or delivery. In animal studies, NSAIDS, including oxaprozin, inhibit prostaglandin synthesis, cause delayed parturition, and increase the incidence of stillbirth.

Data

Human Data

Premature Closure of Fetal Ductus Arteriosus:

Published literature reports that the use of NSAIDs at about 30 weeks of gestation and later in pregnancy may cause premature closure of the fetal ductus arteriosus.

Oligohydramnios/Neonatal Renal Impairment:

Published studies and postmarketing reports describe maternal NSAID use at about 20 weeks gestation or later in pregnancy associated with fetal renal dysfunction leading to oligohydramnios, and in some cases, neonatal renal impairment. These adverse outcomes are seen, on average, after days to weeks of treatment, although oligohydramnios has been infrequently reported as soon as 48 hours after NSAID initiation. In many cases, but not all, the decrease in amniotic fluid was transient and reversible with cessation of the drug. There have been a limited number of case reports of maternal NSAID use and neonatal renal dysfunction without oligohydramnios, some of which were irreversible. Some cases of neonatal renal dysfunction required treatment with invasive procedures, such as exchange transfusion or dialysis.

Methodological limitations of these postmarketing studies and reports include lack of a control group; limited information regarding dose, duration, and timing of drug exposure; and concomitant use of other medications. These limitations preclude establishing a reliable estimate of the risk of adverse fetal and neonatal outcomes with maternal NSAID use. Because the published safety data on neonatal outcomes involved mostly preterm infants, the generalizability of certain reported risks to the full-term infant exposed to NSAIDs through maternal use is uncertain.

Animal data

Teratology studies with oxaprozin were performed in mice, rats, and rabbits in pregnant animals administered oral doses up to 200 mg/kg/day, 200 mg/kg/day, and 30 mg/kg/day, respectively, during the period of organogenesis. In rabbits, malformations were observed at doses greater than or equal to 7.5 mg/kg/day of oxaprozin (0.1 times the maximum recommended human daily dose [MRHD] of 1,200 mg based on body surface area). However, in mice and rats, no drug-related developmental abnormalities or embryo-fetal toxicity were observed at doses up to 50 and 200 mg/kg/day of oxaprozin, respectively (0.2 times and 1.6 times the maximum recommended human daily dose of 1200 mg based on a body surface area comparison, respectively).

In fertility/reproductive studies in rats, 200 mg/kg/day oxaprozin was orally administered to female rats for 14 days prior to mating through lactation day (LD) 2, or from gestation day (GD) 15 through LD 2 and the females were mated with males treated with 200 mg/kg/day oxaprozin for 60 days prior to mating. Oxaprozin administration resulted in failure to deliver and a reduction in live birth index at 200 mg/kg/day (1.6 times the maximum recommended human daily dose of 1,200 mg based on a body surface area comparison).

8.2 Lactation

Risk Summary

There are no data on the presence of oxaprozin in human milk, the effects on the breastfed infant, or the effect on milk production. The developmental and health benefits of breastfeeding should be considered along with the mother’s clinical need for OXAPROZIN CAPSULES and any potential adverse effects on the breastfed infant from the OXAPROZIN CAPSULES or from the underlying maternal condition.

8.3 Females and Males of Reproductive Potential

Infertility

Females

Based on the mechanism of action, the use of prostaglandin-mediated NSAIDs, including OXAPROZIN CAPSULES, may delay or prevent rupture of ovarian follicles, which has been associated with reversible infertility in some women. Published animal studies have shown that administration of prostaglandin synthesis inhibitors has the potential to disrupt prostaglandin-mediated follicular rupture required for ovulation. Small studies in women treated with NSAIDs have also shown a reversible delay in ovulation. Consider withdrawal of NSAIDs, including OXAPROZIN CAPSULES, in women who have difficulties conceiving or who are undergoing investigation of infertility.

Males

Testicular degeneration was observed in beagle dogs treated with 37.5 mg/kg/day (0.7-times the maximum recommended human daily dose based on body surface area) of oxaprozin for 42 days or 6 months [see NONCLINICAL TOXICOLOGY (13.1)]

8.4 Pediatric Use

Safety and effectiveness of oxaprozin, the active component of the OXAPROZIN CAPSULES, have been established for the treatment of the signs and symptoms of juvenile rheumatoid arthritis (JRA) in pediatric patients aged 6 to 16 years. Use of oxaprozin for this indication is supported by evidence from one open label study in 59 pediatric JRA patients and evidence from adequate and well controlled studies in adult rheumatoid arthritis patients.[SEE CLINICAL STUDIES (14.1, 14.2,14.3)].

Gastrointestinal symptoms occurred in pediatric patients at a higher incidence than those historically seen in controlled studies in adults. Of 30 patients in the pediatric JRA trial who continued treatment more than 3 months (19 to 48 weeks range total treatment duration), nine experienced rash on sun-exposed areas of the skin and five of those discontinued treatment [SEE ADVERSE REACTIONS (6.1)].

Safety and effectiveness of OXAPROZIN CAPSULES in pediatric patients below the age of 6 years of age have not been established.

8.5 Geriatric Use

Elderly patients, compared to younger patients, are at greater risk for NSAID-associated serious cardiovascular, gastrointestinal, and/or renal adverse reactions. If the anticipated benefit for the elderly patient outweighs these potential risks, start dosing at the low end of the dosing range, and monitor patients for adverse effects [see WARNINGS AND PRECAUTIONS (5.1, 5.2, 5.3, 5.6, 5.14)].

No adjustment of the dose of OXAPROZIN CAPSULES is necessary in the elderly, although many elderly may need to receive a reduced dose because of low body weight or disorders associated with aging [see CLINICAL PHARMACOLOGY (12.3)].

Of the total number of subjects evaluated in four placebo controlled clinical studies of oxaprozin, 39% were 65 and over, and 11% were 75 and over. No overall differences in safety or effectiveness were observed between these subjects and younger subjects, and other reported clinical experience has not identified differences in responses between the elderly and younger patients, but greater sensitivity of some older individuals cannot be ruled out. Although selected elderly patients in controlled clinical trials tolerated oxaprozin as well as younger patients, caution should be exercised in treating the elderly.

OXAPROZIN CAPSULES is substantially excreted by the kidney, and the risk of toxic reactions to OXAPROZIN CAPSULES may be greater in patients with impaired renal function. Because elderly patients are more likely to have decreased renal function, care should be taken in dose selection, and it may be useful to monitor renal function [see WARNINGS AND PRECAUTIONS (5.6)].

10 OVERDOSAGE

Symptoms following acute NSAID overdosages have been typically limited to lethargy, drowsiness, nausea, vomiting, and epigastric pain, which have been generally reversible with supportive care. Gastrointestinal bleeding has occurred. Hypertension, acute renal failure, respiratory depression, and coma have occurred, but were rare [see WARNINGS AND PRECAUTIONS (5.1, 5.2, 5.4, 5.6)].

Manage patients with symptomatic and supportive care following an NSAID overdosage. There are no specific antidotes. Consider emesis and/or activated charcoal (60 grams to 100 grams in adults, 1 gram to 2 grams per kg of body weight in pediatric patients) and/or osmotic cathartic in symptomatic patients seen within four hours of ingestion or in patients with a large overdosage (5 to 10 times the recommended dosage). Forced diuresis, alkalinization of urine, hemodialysis, or hemoperfusion may not be useful due to high protein binding.
For additional information about overdosage treatment contact a poison control center (1-800-222-1222).

11 DESCRIPTION

OXAPROZIN CAPSULES (oxaprozin) is a nonsteroidal anti-inflammatory drug, available as capsules of 300 mg for oral administration. The chemical name is 4,5-diphenyl-2-oxazole-propionic acid. The molecular weight is 293.32 g/mol. Its molecular formula is C18H15NO3, and it has the following chemical structure.

Oxaprozin is a white to off-white powder with a slight odor and a melting point of 162°C to 163°C. It is slightly soluble in alcohol and insoluble in water, with an octanol/water partition coefficient of 4.8 at physiologic pH (7.4). The pKa in water is 4.3.

The inactive ingredients in OXAPROZIN CAPSULES include: microcrystalline cellulose, pregelatinized corn starch, hypromellose 2910, sodium starch glycolate, stearic acid, and silicon dioxide. OXAPROZIN CAPSULES 300 mg capsules are white opaque capsules imprinted “403” on the cap in black ink.

12 CLINICAL PHARMACOLOGY

.

12.1 Mechanism of Action

Oxaprozin has analgesic, anti-inflammatory, and antipyretic properties.

The mechanism of action of OXAPROZIN CAPSULES, like that of other NSAIDs, is not completely understood but involves inhibition of cyclooxygenase (COX-1 and COX-2).

Oxaprozin is a potent inhibitor of prostaglandin synthesis in vitro. Oxaprozin concentrations reached during therapy have produced in vivo effects. Prostaglandins sensitize afferent nerves and potentiate the action of bradykinin in inducing pain in animal models. Prostaglandins are mediators of inflammation. Because oxaprozin is an inhibitor of prostaglandin synthesis, its mode of action may be due to a decrease of prostaglandins in peripheral tissues.

12.3 Pharmacokinetics

General Pharmacokinetic Characteristics

In dose proportionality studies utilizing 600 mg, 1,200 mg, and 1,800 mg doses, the pharmacokinetics of oxaprozin in healthy subjects demonstrated nonlinear kinetics of both the total and unbound drug in opposite directions, i.e., dose exposure related increase in the clearance of total drug and decrease in the clearance of the unbound drug. Decreased clearance of the unbound drug was related predominantly to a decrease in the volume of distribution of the unbound drug and not an increase inthe elimination half-life. This phenomenon is considered to have minimal impact on drug accumulation upon multiple dosing. The pharmacokinetic parameters of oxaprozin in healthy subjects receiving a single dose of 600 mg (two 300 mg capsules) are presented in Table 3.

Absorption

OXAPROZIN CAPSULES is 95% absorbed after oral administration. Food may reduce the rate of absorption of oxaprozin, but the extent of absorption is unchanged.

Distribution

The apparent volume of distribution (Vd/F) of total oxaprozin is approximately 11 to 17 L/70 kg. Oxaprozin is 99% bound to plasma proteins, primarily to albumin. At therapeutic drug concentrations, the plasma protein binding of oxaprozin is saturable, resulting in a higher proportion of the free drug as the total drug concentration is increased. With increases in single doses or following multiple once-daily dosing, the apparent volume of distribution and clearance of total drug increased, while that of unbound drug decreased due to the effects of nonlinear protein binding.

Oxaprozin penetrates into synovial tissues of rheumatoid arthritis patients with oxaprozin concentrations 2-fold and 3-fold greater than in plasma and synovial fluid, respectively. Oxaprozin is expected to be excreted in human milk based on its physical-chemical properties; however, the amount of oxaprozin excreted in breast milk has not been evaluated.

Elimination

Metabolism

Several oxaprozin metabolites have been identified in human urine or feces.

Oxaprozin is primarily metabolized in the liver, by both microsomal oxidation (65%) and glucuronic acid conjugation (35%). Ester and ether glucuronide are the major conjugated metabolites of oxaprozin. On chronic dosing, metabolites do not accumulate in the plasma of patients with normal renal function. Concentrations of the metabolites in plasma are very low.

Oxaprozin's metabolites do not have significant pharmacologic activity. The major ester and ether glucuronide conjugated metabolites have been evaluated along with oxaprozin in receptor binding studies and in vivo animal models and have demonstrated no activity. A small amount (<5%) of active phenolic metabolites are produced, but the contribution to overall activity is limited.

Excretion

Approximately 5% of the oxaprozin dose is excreted unchanged in the urine. Sixty-five percent (65%) of the dose is excreted in the urine and 35% in the feces as metabolites. Biliary excretion of unchanged oxaprozin is a minor pathway, and enterohepatic recycling of oxaprozin is insignificant. Upon chronic dosing, the accumulation half-life is approximately 22 hours. The elimination half-life is approximately twice the accumulation half-life due to increased binding and decreased clearance at lower concentrations.

Specific Populations

Geriatric: A multiple dose study comparing the pharmacokinetics of oxaprozin (1,200 mg once daily) in 20 young (21 to 44 years) adults and 20 elderly (64 to 83 years) adults did not show any statistically significant differences between age groups.

Pediatric: A population pharmacokinetic study indicated no clinically important age dependent changes in the apparent clearance of unbound oxaprozin between adult rheumatoid arthritis patients (N=40) and juvenile rheumatoid arthritis (JRA) patients (≥6 years, N=44) when adjustments were made for differences in body weight between these patient groups. The extent of protein binding of oxaprozin at various therapeutic total plasma concentrations was also similar between the adult and pediatric patient groups. Pharmacokinetic model-based estimates of daily exposure (AUC0–24) to unbound oxaprozin in JRA patients relative to adult rheumatoid arthritis patients suggest dose to body weight range relationships, as shown in Table 4.

Table 4. Dose to Body Weight Range to Achieve Similar Steady-State Exposure (AUC0–24hr) to Unbound Oxaprozin in JRA Patients Relative to 70 kg Adult Rheumatoid Arthritis Patients Administered Oxaprozin 1,200 mg Once Daily *

Dose (mg) | Body Weight Range (kg)
600 | 22 - 31
900 | 32 - 54
1,200 | > or equal to 55

*Model-based nomogram derived from unbound oxaprozin steady-state plasma concentrations in JRA patients weighing 22.1 – 42.7 kg or ≥45.0 kg administered oxaprozin 600 mg or 1,200 mg once daily for 14 days, respectively.

Race: Pharmacokinetic Differences due to race have not been identified.

Hepatic Impairment: Approximately 95% of oxaprozin is metabolized by the liver. However, patients with well-compensated cirrhosis do not require reduced doses of oxaprozin as compared to patients with normal hepatic function. Nevertheless, monitor patients with severe hepatic dysfunction for adverse reactions.

Renal Impairment: Oxaprozin's renal clearance decreased proportionally with creatinine clearance (CrCL), but since only approximately 5% of oxaprozin dose is excreted unchanged in the urine, the decrease in total body clearance becomes clinically important only in those subjects with highly decreased CrCL. Oxaprozin is not significantly removed from the blood in patients undergoing hemodialysis or continuous ambulatory peritoneal dialysis (CAPD) due to its high protein binding. Oxaprozin plasma protein binding may decrease in patients with severe renal deficiency. Dosage adjustment may be necessary in patients with renal insufficiency [see WARNINGS AND PRECAUTIONS (5.6)].

Cardiac Failure: Well-compensated cardiac failure does not affect the plasma protein binding or the pharmacokinetics of oxaprozin.

Drug Interaction Studies

ACE inhibitors (enalapril): Oxaprozin has been shown to alter the pharmacokinetics of enalapril (significant decrease in dose-adjusted AUC0-24and Cmax) and its active metabolite enalaprilat (significant increase in dose-adjusted AUC0-24) [see DRUG INTERACTIONS (7)].

Aspirin: When oxaprozin was administered with aspirin, the protein binding of oxaprozin was reduced, although the clearance of free oxaprozin was not altered. The clinical significance of this interaction is not known. An in vitro study showed that oxaprozin significantly interfered with the anti-platelet activity of aspirin [see DRUG INTERACTIONS (7)].

Beta-blockers (metoprolol): Subjects receiving 1,200 mg oxaprozin once daily with 100 mg metoprolol twice daily exhibited statistically significant but transient increases in sitting and standing blood pressures after 14 days [see DRUG INTERACTIONS (7)].

Glyburide: Oxaprozin altered the pharmacokinetics of glyburide; however, coadministration of oxaprozin to type II non-insulin dependent diabetic patients did not affect the area under the glucose concentration curve nor the magnitude or duration of control [see DRUG INTERACTIONS (7)].

H2-receptor antagonists (cimetidine, ranitidine): The total clearance of oxaprozin was reduced by 20% in subjects who concurrently received therapeutic doses of cimetidine or ranitidine; no other pharmacokinetic parameter was affected. A change of clearance of this magnitude lies within the range of normal variation and is unlikely to produce a clinically detectable difference in the outcome of therapy.

Lithium: Oxaprozin has produced an elevation in plasma lithium levels and a reduction in renal lithium clearance. The mean minimum lithium concentration increased 15%, and the renal clearance decreased by approximately 20% [see DRUG INTERACTIONS (7)].

Methotrexate: Coadministration of oxaprozin with methotrexate resulted in approximately 36% reduction in apparent oral clearance of methotrexate [see DRUG INTERACTIONS (7)].

Other drugs: The coadministration of oxaprozin and acetaminophen, or conjugated estrogens resulted in no statistically significant changes in pharmacokinetic parameters in single- and/or multiple-dose studies. The interaction of oxaprozin with cardiac glycosides has not been studied.

13 NONCLINICAL TOXICOLOGY

.

13.1 Carcinogenesis, Mutagenesis, Impairment of Fertility

Carcinogenesis

In carcinogenicity studies in rats and mice, oxaprozin administration for 2 years was associated with the exacerbation of liver neoplasms (hepatic adenomas and carcinomas) in male CD mice, but not in female CD mice or male or female rats treated with up to 216 mg/kg via the diet (1.7 times the maximum daily human dose of 1,200 mg based on body surface area). The significance of this species- specific finding to man is unknown.

Mutagenesis

Oxaprozin was not genotoxic in the Ames test, forward mutation in yeast and Chinese hamster ovary (CHO) cells, DNA repair testing in CHO cells, micronucleus testing in mouse bone marrow, chromosomal aberration testing in human lymphocytes, or cell transformation testing in mouse fibroblast.

Impairment of Fertility

Oxaprozin administration was not associated with impairment of fertility in male and female rats at oral doses up to 200 mg/kg/day (1.6 times the maximum recommended human daily dose [MRHD] of 1,200 mg based on a body surface area comparison). However, testicular degeneration was observed in beagle dogs treated with 37.5 mg/kg/day (1.0 times the MRHD based on body surface area) of oxaprozin for 42 days or 6 months, a finding not confirmed in other species. The clinical relevance of this finding is not known.

14 CLINICAL STUDIES

.

14.1 Osteoarthritis

Oxaprozin, the active component of OXAPROZIN CAPSULES, was evaluated for the management of the signs and symptoms of osteoarthritis in a total of 616 patients in active controlled clinical trials against aspirin (N=464), piroxicam (N=102), and other NSAIDs. The active component of OXAPROZIN CAPSULES was given both in variable (600 to 1,200 mg/day) and in fixed (1,200 mg/day) dosing schedules in either single or divided doses. In these trials, oxaprozin was found to be comparable to 2,600 to 3,200 mg/day doses of aspirin or 20 mg/day doses of piroxicam. Oxaprozin was effective both in once daily and in divided dosing schedules. In controlled clinical trials several days of oxaprozin therapy were needed for the drug to reach its full effects [see DOSAGE AND ADMINISTRATION (2.5)].

14.2 Rheumatoid Arthritis

Oxaprozin, the active component of OXAPROZIN CAPSULES, was evaluated for managing the signs and symptoms of rheumatoid arthritis in placebo and active controlled clinical trials in a total of 646 patients. Oxaprozin was given in single or divided daily doses of 600 to 1,800 mg/day and was found to be comparable to 2,600 to 3,900 mg/day of aspirin. At these doses there was a trend (over all trials) for oxaprozin to be more effective and cause fewer gastrointestinal side effects than aspirin.

Oxaprozin was given as a once-a-day dose of 1,200 mg in most of the clinical trials, but larger doses (up to 26 mg/kg or 1,800 mg/day) were used in selected patients. In some patients, OXAPROZIN CAPSULES may be better tolerated in divided doses. Due to its long half-life, several days of oxaprozin were needed for the drug to reach its full effect [see DOSAGE AND ADMINISTRATION (2.5)].

14.3 Juvenile Rheumatoid Arthritis

In a 3-month open label study, 10 to 20 mg/kg/day of oxaprozin, the active component of OXAPROZIN CAPSULES, were administered to 59 JRA patients. Fifty-two patients completed 3 months of treatment with a mean daily dose of 20 mg/kg [SEE CLINICAL PHARMACOLOGY (12.3)].

16 HOW SUPPLIED/STORAGE AND HANDLING

OXAPROZIN capsules 300 mg are white opaque capsule imprinted "403" on the cap in black ink, supplied as:

NDC Number Size
70512-787-60 bottle of 60

Storage

Keep bottles tightly closed. Store at room temperature 20°C to 25°C (68°F to 77°F); excursions permitted between 15°C to 30°C (59°F to 86°F) [see USP Controlled Room Temperature]. Dispense in a tight, light-resistant container with a child-resistant closure. Protect the unit dose from light.

17 PATIENT COUNSELING INFORMATION

Advise the patient to read the FDA-approved patient labeling (Medication Guide) that accompanies each prescription dispensed. Inform patients, families, or their caregivers of the following information before initiating therapy with OXAPROZIN CAPSULES and periodically during the course of ongoing therapy.

Cardiovascular Thrombotic Events

Advise patients to be alert for the symptoms of cardiovascular thrombotic events, including chest pain, shortness of breath, weakness, or slurring of speech, and to report any of these symptoms to their health care provider immediately [ see WARNINGS AND PRECAUTIONS (5.1)].

Gastrointestinal Bleeding, Ulceration, and Perforation

Advise patients to report symptoms of ulcerations and bleeding, including epigastric pain, dyspepsia, melena, and hematemesis to their health care provider. In the setting of concomitant use of low-dose aspirin for cardiac prophylaxis, inform patients of the increased risk for and the signs and symptoms of GI bleeding [ see WARNINGS AND PRECAUTIONS (5.2)].

Hepatotoxicity

Inform patients of the warning signs and symptoms of hepatotoxicity (e.g., nausea, fatigue, lethargy, pruritus, diarrhea, jaundice, right upper quadrant tenderness, and "flu-like" symptoms). If these occur, instruct patients to stop OXAPROZIN CAPSULES and seek immediate medical therapy [ see WARNINGS AND PRECAUTIONS (5.3)].

Heart Failure and Edema

Advise patients to be alert for the symptoms of congestive heart failure including shortness of breath, unexplained weight gain, or edema and to contact their healthcare provider if such symptoms occur [ see WARNINGS AND PRECAUTIONS (5.5)].

Anaphylactic Reactions

Inform patients of the signs of an anaphylactic reaction (e.g., difficulty breathing, swelling of the face or throat). Instruct patients to seek immediate emergency help if these occur [ see CONTRAINDICATIONS (4) and WARNINGS AND PRECAUTIONS (5.7)].

Serious Skin Reactions, including DRESS

Advise patients to stop taking OXAPROZIN CAPSULES immediately if they develop any type of rash or fever and to contact their healthcare provider as soon as possible [ see WARNINGS AND PRECAUTIONS (5.9, 5.10)].

Female Fertility

Advise females of reproductive potential who desire pregnancy that NSAIDs, including OXAPROZIN CAPSULES, may be associated with a reversible delay in ovulation [ see USE IN SPECIFIC POPULATIONS (8.3)].

Fetal Toxicity

Inform pregnant women to avoid use of OXAPROZIN CAPSULES and other NSAIDs starting at 30 weeks gestation because of the risk of the premature closing of the fetal ductus arteriosus. If treatment with OXAPROZIN CAPSULES is needed for a pregnant woman between about 20 to 30 weeks gestation, advise her that she may need to be monitored for oligohydramnios, if treatment continues for longer than 48 hours [ see WARNINGS AND PRECAUTIONS (5.11) and USE IN SPECIFIC POPULATIONS (8.1)].

Avoid Concomitant Use of NSAIDs

Inform patients that the concomitant use of OXAPROZIN CAPSULES with other NSAIDs or salicylates (e.g., diflunisal, salsalate) is not recommended due to the increased risk of gastrointestinal toxicity, and little or no increase in efficacy [ see WARNINGS AND PRECAUTIONS (5.2) and DRUG INTERACTIONS (7)]. Alert patients that NSAIDs may be present in "over the counter" medications for treatment of colds, fever, or insomnia.

Use of NSAIDS and Low-Dose Aspirin

Inform patients not to use low-dose aspirin concomitantly with OXAPROZIN CAPSULES until they talk to their healthcare provider [ see DRUG INTERACTIONS (7)].

This product’s labeling may have been updated. For the most recent prescribing information, please visit www.solameds.us.

Manufactured for:

Sola Pharmaceuticals LLC

Baton Rouge, LA 70810

Medication Guide

OXAPROZIN CAPSULES

OXAPROZIN CAPSULES is a prescription mediciine that contains oxaprozin (a non-steroidal anti-inflammatory drug [NSADI])

What is the most important information I should know about OXAPROZIN CAPSULES and medicines called nonsteroidal anti-inflammatory drugs (NSAIDs)?

OXAPROZIN CAPSULES can cause serious side effects, including:

- Increased risk of a heart attack or stroke that can lead to death. This risk may happen early in treatment and may increase:
- with increasing doses of NSAIDs
- with longer use of NSAIDs

Do not take OXAPROZIN CAPSULES right before or after a heart surgery called a "coronary artery bypass graft (CABG)".

Avoid taking OXAPROZIN CAPSULES after a recent heart attack, unless your healthcare provider tells you to. You may have an increased risk of another heart attack if you take OXAPROZIN CAPSULES after a recent heart attack.

- Increased risk of bleeding, ulcers, and tears (perforation) of the esophagus (tube leading from the mouth to the stomach), stomach and intestines:
- anytime during use
- without warning symptoms
- that may cause death

- The risk of getting an ulcer or bleeding increases with:
- history of stomach ulcers, or stomach or intestinal bleeding with use of NSAIDs
- taking medicines called "corticosteroids", "antiplatelet drugs", "anticoagulants", "selective serotonin reuptak inhibitors (SSRIs)", "serotonin norepinephrine reuptake inhibitors (SNRIs)"

- increasing doses of NSAIDs
- longer use of NSAIDs
- smoking
- drinking alcohol

- older age
- poor health
- advanced liver disease
- bleeding problems

OXAPROZIN CAPSULES should only be used:

- exactly as prescribed
- at the lowest dose possible for your treatment
- for the shortest time needed

What is OXAPROZIN CAPSULES?

OXAPROZIN CAPSULES is a prescription medicine used:

- for relief of the signs and symptoms of osteoarthritis
- for relief of the signs and symptoms of rheumatoid arthritis
- for relief of the signs and symptoms of juvenile rheumatoid arthritis.

It is not known if OXAPROZIN CAPSULES is safe and effective in children below 6 years of age.

Do not take OXAPROZIN CAPSULES:

- if you are allergic to oxaprozin or to any of the ingredients in OXAPROZIN CAPSULES. See the end of this Medication Guide for a complete list of ingredients in OXAPROZIN CAPSULES.
- if you have had an asthma attack, hives, or other allergic reaction after taking aspirin or any other NSAIDs. Severe allergic reactions that have sometimes led to death have happened in people with a history of allergic reactions to NSAIDs.
- right before or after heart bypass surgery.

Before taking OXAPROZIN CAPSULES, tell your healthcare provider about all of your or your child's medical conditions, including if you:

- have heart problems
- have bleeding problems
- have or have had ulcers
- have liver or kidney problems
- have high blood pressure
- have asthma • are pregnant or plan to become pregnant. Taking OXAPROZIN CAPSULES at about 20 weeks of pregnancy or later may harm your unborn baby.
  - If you need to take OXAPROZIN CAPSULES for more than 2 days when you are between 20 and 30 weeks of pregnancy, your healthcare provider may need to monitor the amount of fluid in your womb around your baby. You should not take OXAPROZIN CAPSULES after about 30 weeks of pregnancy.
- OXAPROZIN CAPSULES may cause fertility problems in females, which may affect your ability to become pregnant. Talk to your healthcare provider if this is a concern for you.
- are breastfeeding or plan to breastfeed. Talk to your healthcare provider about the best way to feed your baby

during treatment with OXAPROZIN CAPSULES.

Tell your healthcare provider about all of the medicines you or your child take, including prescription or over-the-counter medicines, vitamins or herbal supplements.

OXAPROZIN CAPSULES and some other medicines can interact with each other and cause serious side effects.

Do not start taking any new medicine without talking to your healthcare provider first.

How should I take OXAPROZIN CAPSULES?

- Take OXAPROZIN CAPSULES exactly as your healthcare provider tells you to take it.
- If you take too much OXAPROZIN CAPSULES, call your healthcare provider or Poison Control Center at 1-800-222-1222, or go to the nearest hospital emergency room right away.

What are the possible side effects of OXAPROZIN CAPSULES?

OXAPROZIN CAPSULES may cause serious side effects, including:

See " WHAT IS THE MOST IMPORTANT INFORMATION I SHOULD KNOW ABOUT OXAPROZIN CAPSULES AND MEDICINES CALLED NONSTEROIDAL ANTI-INFLAMMATORY DRUGS (NSAIDS)?"

- liver problems including liver failure
- new or worse high blood pressure
- heart failure
- kidney problems including kidney failure
- increase in blood potassium level (hyperkalemia)
- life-threatening allergic reactions
- asthma attacks in people who have asthma
- serious skin reactions, including life-threatening skin reactions
- low red blood cells (anemia)
- skin sensitivity to sunlight

Other side effects of OXAPROZIN CAPSULES include: constipation, diarrhea, indigestion, nausea, and rash.

Get emergency help right away if you get any of the following symptoms:

- shortness of breath or trouble breathing
- chest pain
- weakness in one part or side of your body

- slurred speech
- swelling of the face or throat

Stop taking your OXAPROZIN CAPSULES and call your healthcare provider right away if you get any of the following symptoms:

- nausea
- more tired or weaker than usual
- diarrhea
- itching
- your skin or eyes look yellow
- indigestion or stomach pain
- flu-like symptoms

- vomit blood
- there is blood in your bowel movement or it is black and sticky like tar
- unusual weight gain
- skin rash or blisters with fever
- swelling of the arms, legs, hands and feet

These are not all the possible side effects of OXAPROZIN CAPSULES.

Call your doctor for medical advice about side effects. You may report side effects to FDA at 1-800-FDA-1088.

Other information about NSAIDs

- Aspirin is an NSAID but it does not increase the chance of a heart attack. Aspirin can cause bleeding in the brain, stomach, and intestines. Aspirin can also cause ulcers in the stomach and intestines.
- Some NSAIDs are sold in lower doses without a prescription (over-the-counter). Talk to your healthcare provider before using over-the-counter NSAIDs for more than 10 days.

How should I store OXAPROZIN CAPSULES?

- Store OXAPROZIN CAPSULES at room temperature between 68°F to 77°F (20°C to 25°C).
- Keep the OXAPROZIN CAPSULES bottles tightly closed.
- Protect the bottle from light.

Keep OXAPROZIN CAPSULES and all medicines out of the reach of children.

General information about the safe and effective use of OXAPROZIN CAPSULES

Medicines are sometimes prescribed for purposes other than those listed in a Medication Guide. Do not use OXAPROZIN CAPSULES for a condition for which it was not prescribed. Do not give OXAPROZIN CAPSULES to other people, even if they have the same symptoms that you have. It may harm them. You can ask your pharmacist or healthcare provider for information about OXAPROZIN CAPSULES that is written for health professionals.

What are the ingredients in OXAPROZIN CAPSULES?

Active ingredient: oxaprozin

Inactive ingredients: microcrystalline cellulose, pregelatinized corn starch, hypromellose 2910, sodium starch

glycolate, stearic acid, and silicon dioxide.

Manufactured for:

Sola Pharmaceuticals, LLC

Baton Rouge, LA 70810

For more information, call 1-866-747-7365

This Medication Guide has been approved by the U.S. Food and Drug Administration. Issued: 10/2023

This product's labeling may have been updated. For the most recent prescribing information, please visit www.solameds.us.
Manufactured for:
SOLA
Pharmaceuticals
Baton Rouge, LA 70810

PRINCIPAL DISPLAY PANEL - 300 MG CAPSULE BOTTLE LABEL:

ALWAYS DISPENSE WITH MEDICATION GUIDE

NDC 70512-787-60

Sola Pharmaceuticals, LLC

Oxaprozin Capsules

300 mg

60 Capsules
Rx only